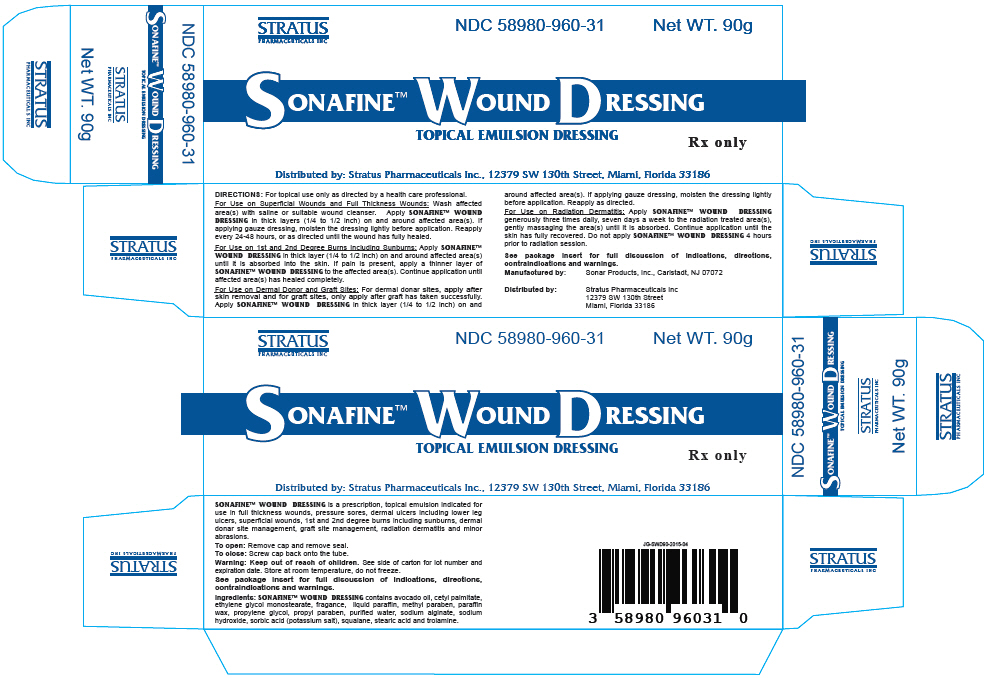 DRUG LABEL: Sonafine Wound Dressing
NDC: 58980-960 | Form: EMULSION
Manufacturer: Stratus Pharmaceuticals
Category: other | Type: MEDICAL DEVICE
Date: 20250411
INACTIVE INGREDIENTS: Mineral Oil; Stearic Acid; Paraffin; Squalane; Avocado Oil; Cetyl Palmitate; Glycol Stearate; Methylparaben; Propylparaben; Water; Propylene Glycol; Sodium Alginate; Trolamine; Sodium Hydroxide; Potassium Sorbate

SONAFINE™ WOUND DRESSING

TOPICAL EMULSION DRESSING

Description

SONAFINE™ WOUND DRESSING is a water-based emulsion formulated for the dressing and management of superficial wounds, minor abrasions, dermal ulcers, donor sites, 1st and 2nd degree burns, including sunburns, and radiation dermatitis. When applied properly to a wound SONAFINE™ WOUND DRESSING provides an optimum moist environment for the healing process and isolates the wound from harmful germs and other external contamination.

Indications and Usage

SONAFINE™ WOUND DRESSING is indicated for use in: Full Thickness Wounds, Pressure Sores, Dermal Ulcers including Lower Leg Ulcers, Superficial Wounds, 1st and 2nd Degree Burns, Including Sunburns, Dermal Donor and Graft Site Management, Radiation Dermatitis and Minor Abrasions

Contraindications

SONAFINE™ WOUND DRESSING is contraindicated for use on bleeding wounds, skin rashes related to food or medicine allergies and when an allergy to one of the ingredients is known.

Warnings

In radiation therapy SONAFINE™ WOUND DRESSING may be applied as directed by the treating physician. Do not apply 4 hours prior to a radiation session.

Do not apply SONAFINE™ WOUND DRESSING to dermal grafts until after the graft has successfully taken.

Keep out of the reach of children.

Precautions and Observations

For the treatment of any dermal wound, consult a physician. Use SONAFINE™ WOUND DRESSING only as directed.

SONAFINE™ WOUND DRESSING is nontoxic, it is for topical use only and should not be ingested or taken internally.

SONAFINE™ WOUND DRESSING does not contain a sunscreen and should not be used prior to extended exposure to the sun.

The use of SONAFINE™ WOUND DRESSING on skin rashes due to allergies has not been studied sufficiently and therefore is not recommended.

Following the application of SONAFINE™ WOUND DRESSING a temporary tingling sensation may occur (10 to 15 minutes). If clinically indicated, use of SONAFINE™ WOUND DRESSING may be continued during the anti-infective therapy.

If the condition does not improve within 10-14 days, consult a physician.

SONAFINE™ WOUND DRESSING may dissolve fuchsin when this dye is used to define the margins of the radiation fields to be treated.

Instructions for Use

SONAFINE™ WOUND DRESSING is for topical use only as directed by a healthcare professional.

Wounds, Abrasions, Full Thickness Wounds, Dermal Graft Site Management and Donor Site Management

Wash the affected area(s) with saline, clean water or suitable wound cleanser.

Apply SONAFINE™ WOUND DRESSING on and around the affected area(s) in thick layers ¼ to ½ inch thick.

If applying gauze dressing, moisten the dressing lightly before application.

Reapply SONAFINE™ WOUND DRESSING as described above every 24 to 48 hours or as directed until the wound or lesion has healed fully.

For donor site management, apply SONAFINE™ WOUND DRESSING after skin removal and cover with a moist dressing. Reapply as directed.

For dermal graft site management apply SONAFINE™ WOUND DRESSING to the graft site only after the graft has taken successfully. SONAFINE™ WOUND DRESSING can be washed away with a saline solution or clean water without causing damage to the newly formed tissues.

1st and 2nd Degree Burns Including Sunburns

Before any application of SONAFINE™ WOUND DRESSING to burns take precaution in removing any clothing in the affected area(s).

Apply SONAFINE™ WOUND DRESSING as soon as possible on and around the affected area(s) in a thick ¼ to ½ inch layer until the skin no longer absorbs the product. A white waxy residue may remain. If pain from the burn persists, apply thinner layers of SONAFINE™ WOUND DRESSING until the pain has ceased.

Continue to apply SONAFINE™ WOUND DRESSING until the affected area(s) has healed completely.

Application of SONAFINE™ WOUND DRESSING to the affected area(s) should continue during any subsequent physical therapy treatments.

Radiation Dermatitis

Apply a generous amount of SONAFINE™ WOUND DRESSING three times per day, seven days a week to the treated area(s), gently massaging the area(s) until SONAFINE™ WOUND DRESSING is completely absorbed.

SONAFINE™ WOUND DRESSING may be applied as indicated by the treating physician (see Warnings).

Continue to apply SONAFINE™ WOUND DRESSING as described above until the skin has fully recovered.

Do not interrupt applications during the course of radiation therapy, even for one day.

Do not apply SONAFINE™ WOUND DRESSING 4 hours prior to a radiation session.

Ingredients

SONAFINE™ WOUND DRESSING contains avocado oil, cetyl palmitate, ethylene glycol monostearate, fragance, liquid paraffin, methyl paraben, paraffin wax, propylene glycol, propyl paraben, purified water, sodium alginate, sodium hydroxide, sorbic acid (potassium salt), squalane, stearic acid and trolamine.

How Supplied

SONAFINE™ WOUND DRESSING is supplied in tubes in the following sizes:

45gram tube, NDC# 58980-960-12
90gram tube, NDC# 58980-960-31

STORAGE AND HANDLING

Store at room temperature, do not freeze.

Rx ONLY- Prescription Medical Device: Federal Law restricts this device to sale by or on the order of a physician (or properly licensed practitioner).

Manufactured by:
Sonar Products Inc
Carlstadt, NJ 07072

Distributed by:
Stratus Pharmaceuticals Inc
12379 SW 130th Street
Miami, FL 33186

For additional information:
Contact Customer Service at:
Toll Free - 1-800-442-7882

www.stratuspharmaceuticals.com

JG-SWDIN-I2015-04

PRINCIPAL DISPLAY PANEL - 90 g Tube Box

STRATUS
PHARMACEUTICALS INC
NDC 58980-960-31
Net WT. 90g

SONAFINE™ WOUND DRESSING
TOPICAL EMULSION DRESSING

Rx only

Distributed by: Stratus Pharmaceuticals Inc., 12379 SW 130th Street, Miami, Florida 33186